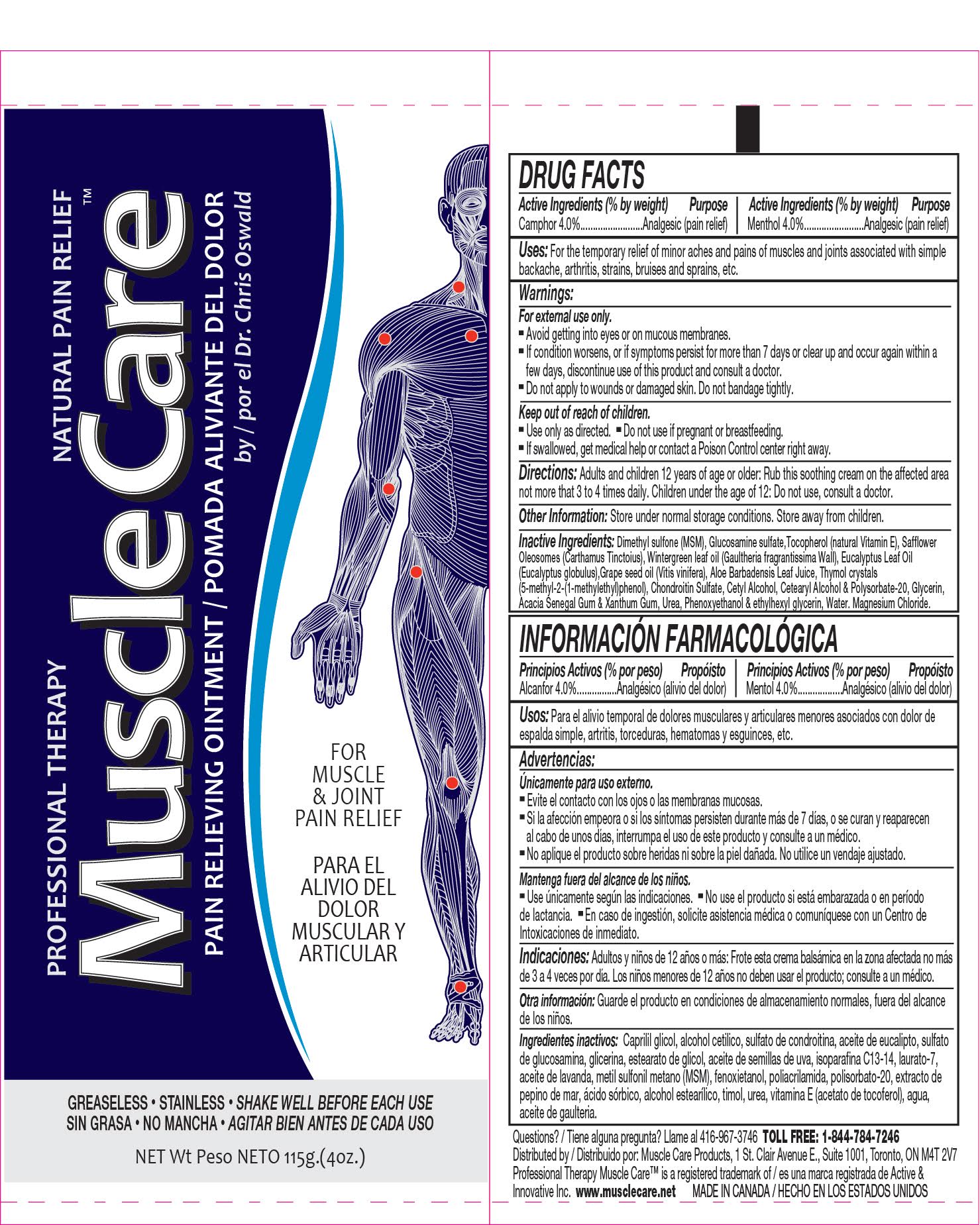 DRUG LABEL: Professional Therapy MuscleCare Pain Relieving
NDC: 70039-300 | Form: OINTMENT
Manufacturer: Active and Innovative Inc.
Category: otc | Type: HUMAN OTC DRUG LABEL
Date: 20250123

ACTIVE INGREDIENTS: MENTHOL 40 mg/1 g; CAMPHOR (SYNTHETIC) 40 mg/1 g
INACTIVE INGREDIENTS: DIMETHYL SULFONE; GLUCOSAMINE SULFATE; METHYL SALICYLATE; EUCALYPTUS OIL; ALOE VERA LEAF; THYMOL; XANTHAN GUM; UREA; PHENOXYETHANOL; ACACIA; GRAPE SEED OIL; TOCOPHEROL; CARTHAMUS TINCTORIUS (SAFFLOWER) OLEOSOMES; CHONDROITIN SULFATE (CHICKEN); CETYL ALCOHOL; CETOSTEARYL ALCOHOL; POLYSORBATE 20; GLYCERIN; ETHYLHEXYLGLYCERIN; WATER; MAGNESIUM CHLORIDE

Professional Therapy MuscleCare pain relieving ointment, 4 oz.

PURPOSE

For muscle and joint pain relief

ACTIVE INGREDIENTS (% BY WEIGHT) PURPOSE

Menthol 4.0%...........................Analgesic (pain relief)

Camphor 4.0%........................Analgesic (pain relief)

USE:

For the temporary relief of minor aches and pains of muscles and joints associated with simple backache, arthritis, strains, bruises and sprains, etc.

WARNINGS:

For external use only.

Avoid getting into eyes or on mucous membranes.

If condition worsens, or if symptoms persist for more than 7 days or clear up and occur again within a few days, discontinue use of this product and consult a doctor.

Do not apply to wounds or damaged skin. Do not bandage tightly.

KEEP OUT OF REACH OF CHILDREN:

Use only as directed.

Do not use if you are pregnant or breastfeeding.

If swallowed, get medical help or contact a Poison Control center right away.

DOSAGE AND ADMINISTRATION

Directions: Adults and children 12 years of age or older: Rub this soothing cream onto the effected area not more than 3 to 4 times daily. Children under the age of 12: Do not use, consult a doctor.

Other Information: Store under normal storage conditions. Store away from children.

INACTIVE INGREDIENT

Inactive Ingredients:Dimethyl sulfone (MSM), Gluosamine sulfate, Tocopherol (natural Vitamin E), Safflower Oleosomes (Carthamus Tinctorius), Wintergreen leaf oil (Gaultheria fragrantissima Wall), Eucalyptus leaf oil 9Eucalyptus globus), Grape seed oil (Vitis vinifera), Aloe babadensis leaf juice, Thymol crystals (5-methyl-2-(1-methylethyl)phenol), Chondroitin sulfate, Cetyl alcohol, Cetearyl alcohol & Polysorbate-20, Glycerin, Acacia Senegal Gum & Xanthan Gum, Urea, Phenoxyethanol & ethylhexyl glycerin, Water, Magnesium chloride.